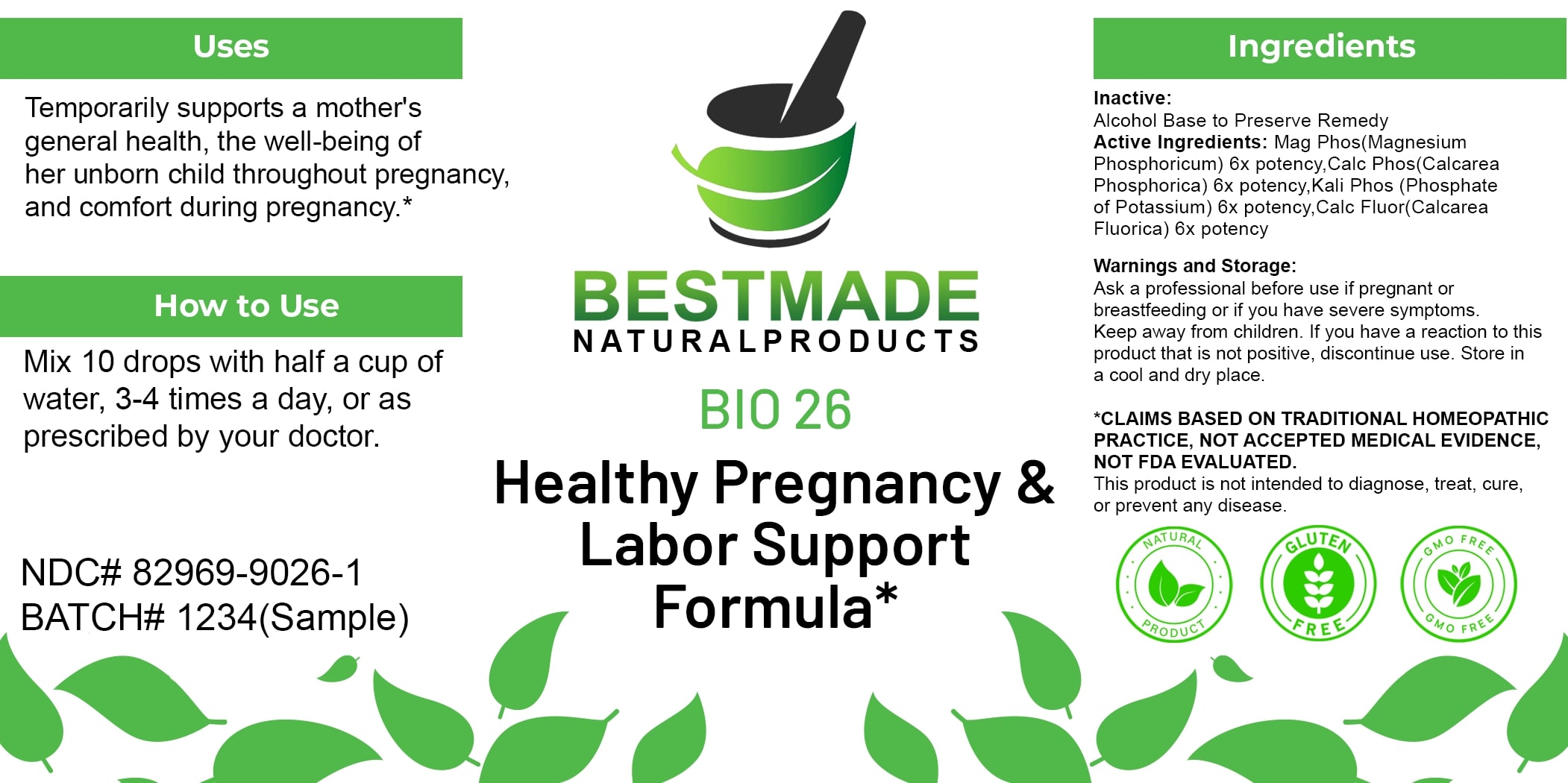 DRUG LABEL: Bestmade Natural Products BIO26
NDC: 82969-9026 | Form: LIQUID
Manufacturer: Bestmade Natural Products
Category: homeopathic | Type: HUMAN OTC DRUG LABEL
Date: 20250323

ACTIVE INGREDIENTS: MAGNESIUM PHOSPHATE, DIBASIC TRIHYDRATE 6 [hp_X]/6 [hp_X]; CALCIUM FLUORIDE 6 [hp_X]/6 [hp_X]; TRIBASIC CALCIUM PHOSPHATE 6 [hp_X]/6 [hp_X]; DIBASIC POTASSIUM PHOSPHATE 6 [hp_X]/6 [hp_X]
INACTIVE INGREDIENTS: ALCOHOL 6 [hp_X]/6 [hp_X]

BIO 26 Healthy Pregnancy & Labor Support*

DOSAGE AND ADMINISTRATION

How to Use

Mix 10 drops with half a cup of water, 3-4 times a day, or as prescribed by your doctor.

Inactive:

Alcohol Base to Preserve Product

ACTIVE INGREDIENT

Active Ingredients: Mag Phos(Magnesium Phosphoricum) 6x potency, Calc Phos(Calcarea Phosphorica) 6x potency, Kali Phos(Phosphate of Potassium) 6x potency, Calc Fluor(Calcarea Fluorica) 6x potency

Uses

Temporarily supports a mother's general health, the well-being of her unborn child throughout pregnancy, and comfort during pregnancy.*

*CLAIMS BASED ON TRADITIONAL HOMEOPATHIC PRACTICE, NOT ACCEPTED MEDICAL EVIDENCE, NOT FDA EVALUATED.

This product is not intended to diagnose, treat, cure, or prevent any disease.

Uses

Temporarily supports a mother's general health, the well-being of her unborn child throughout pregnancy, and comfort during pregnancy.*

*CLAIMS BASED ON TRADITIONAL HOMEOPATHIC PRACTICE, NOT ACCEPTED MEDICAL EVIDENCE, NOT FDA EVALUATED.

This product is not intended to diagnose, treat, cure, or prevent any disease.

KEEP OUT OF REACH OF CHILDREN

Warnings and Storage:

Ask a professional before use if pregnant or breastfeeding or if you have severe symptoms. Keep away from children. If you have a reaction to this product that is not positive, discontinue use. Store in a cool and dry place.

Warnings and Storage:

Ask a professional before use if pregnant or breastfeeding or if you have severe symptoms. Keep away from children. If you have a reaction to this product that is not positive, discontinue use. Store in a cool and dry place.

*CLAIMS BASED ON TRADITIONAL HOMEOPATHIC PRACTICE, NOT ACCEPTED MEDICAL EVIDENCE NOT FDA EVALUATED.

This product is not intended to diagnose, treat, cure, or prevent any disease.

Entire package label